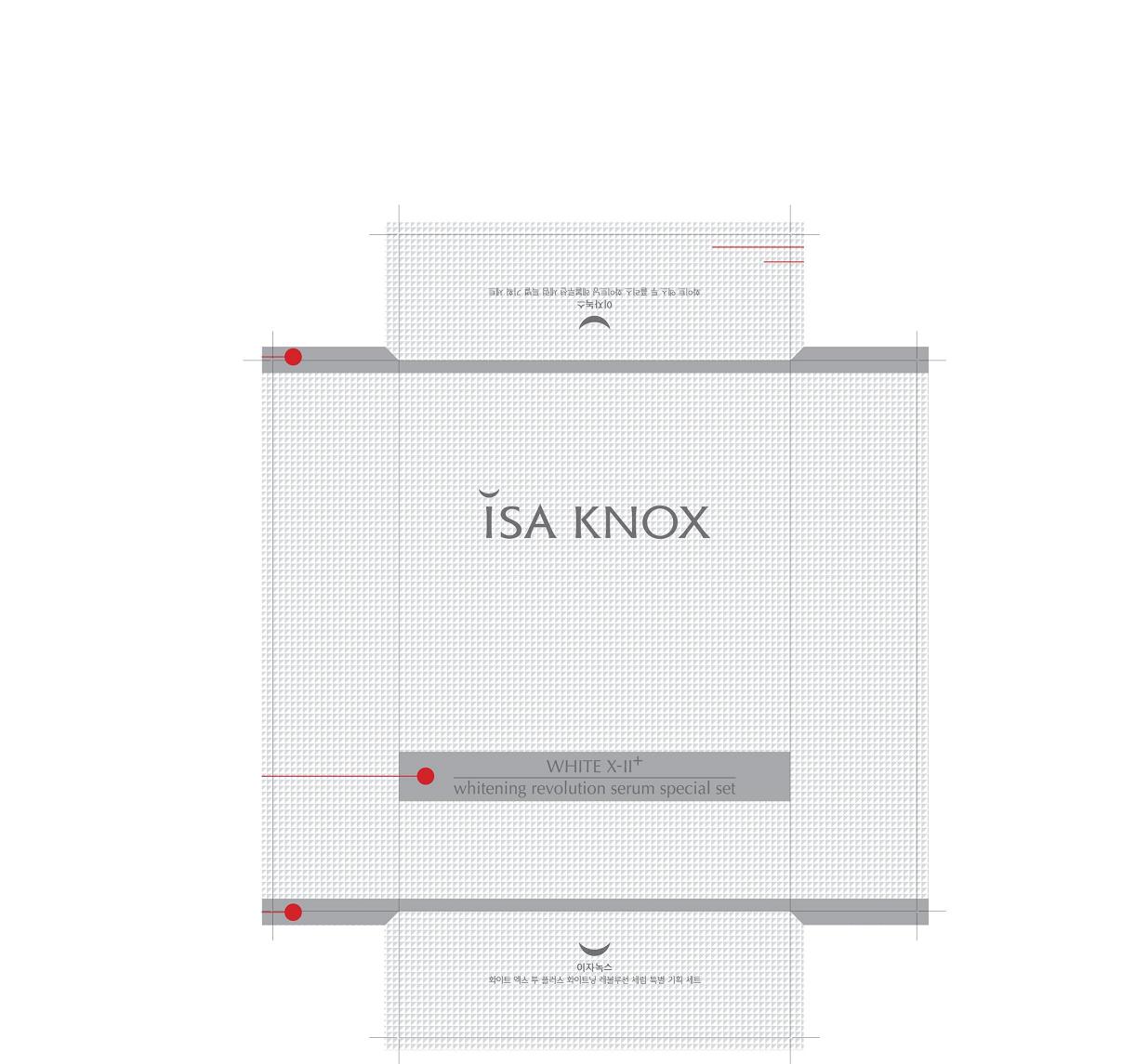 DRUG LABEL: ISA KNOX WXII PLUS WHITENING REVOLUTION SERUM
NDC: 53208-424 | Form: CREAM
Manufacturer: LG Household and Healthcare, Inc.
Category: otc | Type: HUMAN OTC DRUG LABEL
Date: 20100423

ACTIVE INGREDIENTS: DIOSMETIN 0.11 mL/100 mL
INACTIVE INGREDIENTS: WATER; 2-ETHYLHEXANOIC ACID; DIPROPYLENE GLYCOL; DOCOSANOL; CETOSTEARYL ALCOHOL; CYCLOMETHICONE 5; ALCOHOL; FILIPENDULA ULMARIA FLOWER; BETAINE; DIMETHICONE; METHYLPARABEN; TROLAMINE; GLYCERYL MONOSTEARATE; PROPYLPARABEN; CARBOMER 934; ETHYLPARABEN; EDETATE TRISODIUM; FD&C YELLOW NO. 5

Drug Facts

ACTIVE INGREDIENT

DIOSMETIN 0.11g/100g

WARNINGS AND PRECAUTIONS

For external use only

Keep out of reach of children. Is swallowed, get medical help or contact a Poison Control Center right away.

WHEN USING

Keep out of eyes. Rinse with water to remove.